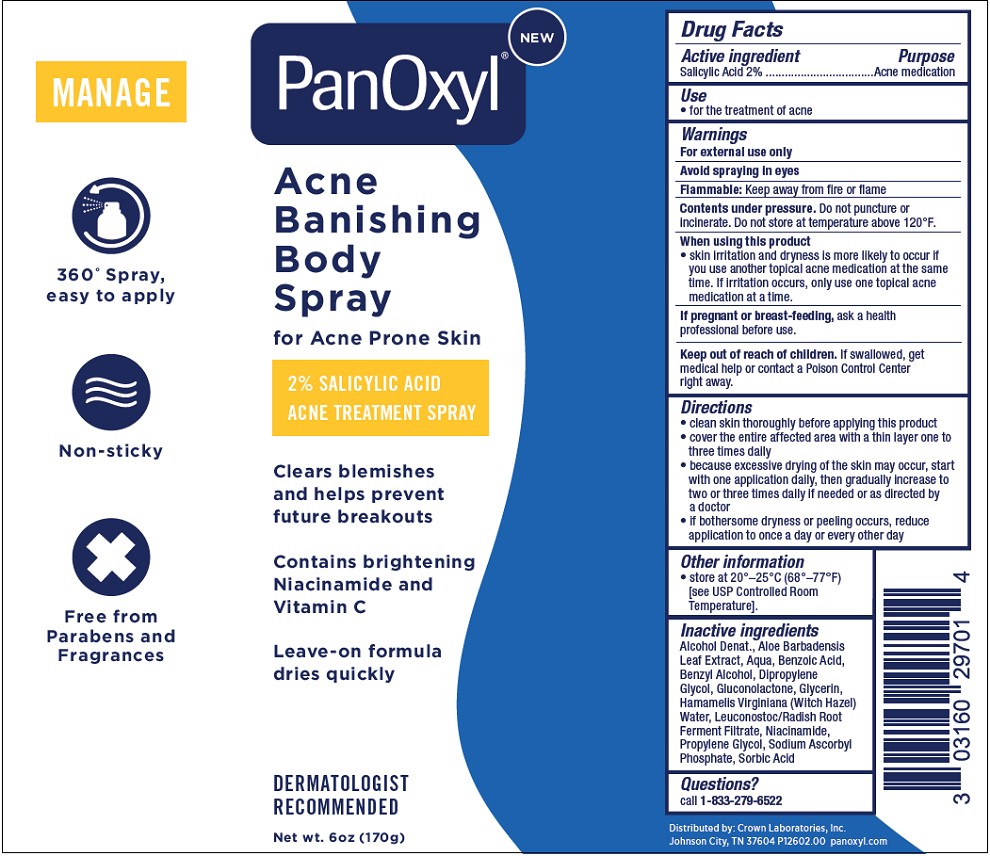 DRUG LABEL: PanOxyl Acne Banishing Body (Spray)
NDC: 0316-0297 | Form: AEROSOL, SPRAY
Manufacturer: Crown Laboratories, Inc.
Category: otc | Type: HUMAN OTC DRUG LABEL
Date: 20260105

ACTIVE INGREDIENTS: SALICYLIC ACID 2 g/100 g
INACTIVE INGREDIENTS: LEUCONOSTOC/RADISH ROOT FERMENT FILTRATE; GLUCONOLACTONE; PROPYLENE GLYCOL; WATER; HAMAMELIS VIRGINIANA TOP WATER; NIACINAMIDE; ALCOHOL; GLYCERIN; DIPROPYLENE GLYCOL; BENZOIC ACID; SODIUM ASCORBYL PHOSPHATE; SORBIC ACID; ALOE VERA LEAF; BENZYL ALCOHOL

PanOxyl Acne Banishing Body Spray

Active ingredient

Salicylic Acid 2%

Purpose

Acne Medication

Use

- for the treatment of acne

Warnings

For external use only

Avoid spraying in eyes

Flammable: Keep away from fire or flame

Contents under pressure. Do not puncture or incinerate. Do not store at temperature above 120°F.

When using this product

- skin irritation and dryness is more likely to occur if you use another topical acne medication at the same time. If irritation occurs, only use one topical acne medication at a time.

If pregnant or breast-feeding,

ask a health professional before use.

Keep out of reach of children.

If swallowed, get medical help or contact a Poison Control Center right away.

Directions

- clean the skin thoroughly before applying this product
- cover the entire affected area with a thin layer one to three times daily
- because excessive drying of the skin may occur, start with one application daily, then gradually increase to two or three times daily if needed or as directed by a doctor
- if bothersome dryness or peeling occurs, reduce application to once a day or every other day

Other information

- Store at 20o - 25oC (68o - 77oF) [see USP Controlled Room Temperature].

Inactive ingredients

Alcohol Denat., Aloe Barbadensis Leaf Extract, Aqua, Benzoic Acid, Benzyl Alcohol, Dipropylene Glycol, Gluconolactone, Glycerin, Hamamelis Virginiana (Witch Hazel) Water, Leuconostoc/Radish Root Ferment Filtrate, Niacinamide, Propylene Glycol, Sodium Ascorbyl Phosphate, Sorbic Acid

Questions?

call 1-833-279-6522

PanOxyl Acne Banishing Body Spray

NEW

PanOxyl

Acne Banishing Body Spray

for Acne Prone Skin

2% SALICYLIC ACID

ACNE TREATMENT SPRAY

Clears blemishes and helps prevent future breakouts

Contains brightening Niacinamide and Vitamin C

Leave-on formula dries quickly

DERMATOLIGST RECOMMENDED

Net wt. 6oz (170g)

Distributed by: Crown Laboratories, Inc.

Johnson City, TN 37604

P12602.00

panoxyl.com